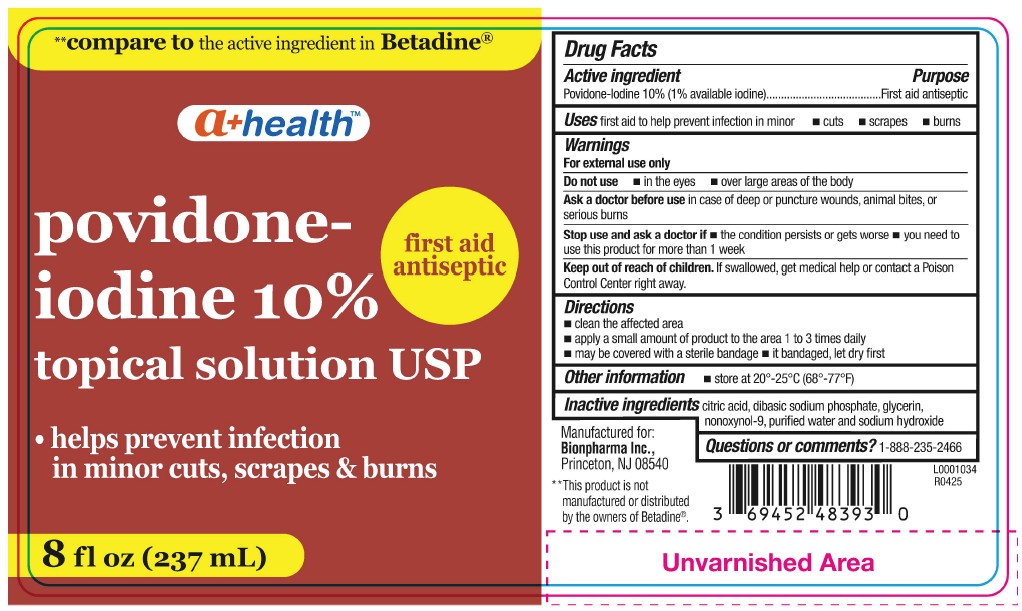 DRUG LABEL: povidone-iodine 10%
NDC: 69452-483 | Form: SOLUTION
Manufacturer: BIONPHARMA INC.
Category: otc | Type: HUMAN OTC DRUG LABEL
Date: 20251006

ACTIVE INGREDIENTS: POVIDONE-IODINE 10 mg/1 mL
INACTIVE INGREDIENTS: WATER; NONOXYNOL-9; SODIUM HYDROXIDE; GLYCERIN; CITRIC ACID; SODIUM PHOSPHATE, DIBASIC, MONOHYDRATE

a+ health- povidone-iodine topical solution

Drug Facts

Active ingredient

Povidone-iodine, 10% (1% available iodine)

Purpose

First aid antiseptic

Uses

first aid to help prevent infection in minor • cuts • scrapes • burns

Warnings

For exmrnal use only

Do not use

• in the eyes • over large areas of the body

Ask a doctor before use

in case of deep or puncture wounds, animal bites, or serious burns

Stop use and ask a doctor if

• the condition persists or gets worse • you need to use this product for more than 1 week

Keep out of reach of children.

if swallowed, get medical help or contact a Poison Control Center right away.

Directions

• clean the affected area
• apply a small amount of product to the area 1 to 3 times daily
• may be covered with a sterile bandage • it bandaged, let dry first

Other information

• store at 20°-25°C (68°-77°F)

Inactive ingredients

citric acid, dibasic sodium phosphate, glycerin, nonoxynol-9, purified water and sodium hydroxide

Questions or comments?

1-888-235-2466

Manufactured for:

Bionpharma Inc.,
Princeton, NJ 08540

**This product is not manufactured or dislributed by the owners of Betadine®

L0001034
R0425

8 fl oz (237 mL) Bottle

** compare to the active ingredient in Betadine®

a+ healthTM

first aid

antiseptic

povidone-

iodine 10%

topical solution USP

• helps prevent infection

in minor cuts, scrapes & burns

8 fl oz (237 mL)